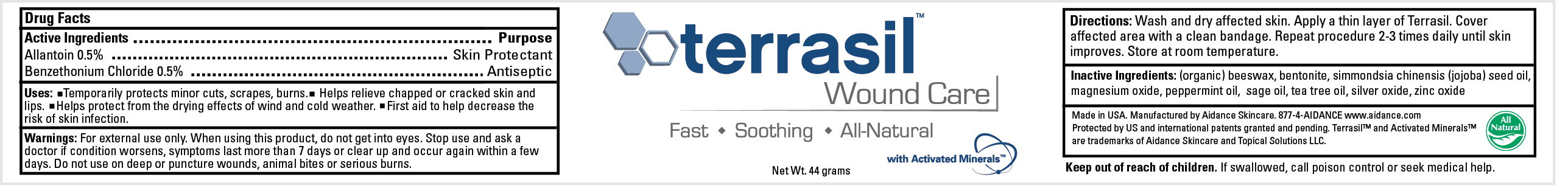 DRUG LABEL: TERRASIL WOUND CARE
								
NDC: 24909-115 | Form: OINTMENT
Manufacturer: Aidance Skincare & Topical Solutions, LLC
Category: otc | Type: HUMAN OTC DRUG LABEL
Date: 20120120

ACTIVE INGREDIENTS: Allantoin 0.5 g/100 g; Benzethonium Chloride 0.5 g/100 g
INACTIVE INGREDIENTS: WHITE WAX; BENTONITE; JOJOBA OIL; MAGNESIUM OXIDE;  PEPPERMINT OIL; SAGE OIL; SILVER OXIDE; ZINC OXIDE

Drug Facts

Active Ingredient

Allantoin 0.5%

Benzethonium Chloride 0.5%

Purpose

Allantoin - Skin Protectant

Benzethonium Chloride - Antiseptic

Uses

Temporarily protects minor cuts, scrapes, burns. Helps relieve chapped or cracked skin and lips. Helps protect from the drying effects of wind and cold weather. First aid to help decrease the risk of skin infection.

Warnings

For external use only. When using this product, do not get into eyes. Stop use and ask a doctor if condition worsens, symptoms last more than 7 days or clear up and occur again within a few days. Do not use on deep or puncture wounds, animal bites or serious burns.

Keep out of reach of children.

If swallowed, call poison control or seek medical help.

Directions

Wash and dry affected skin. Apply a thin layer of Terrasil. Cover affected area with a clean bandage. Repeat procedure 2-3 times daily until skin improves. Store at room temperature.

Inactive Ingredients

(Organic) Beeswax, Bentonite, Simmondsia Chinensis (Jojoba) Seed Oil, Magnesium Oxide, Peppermint Oil, Sage Oil, Silver Oxide,
Zinc Oxide